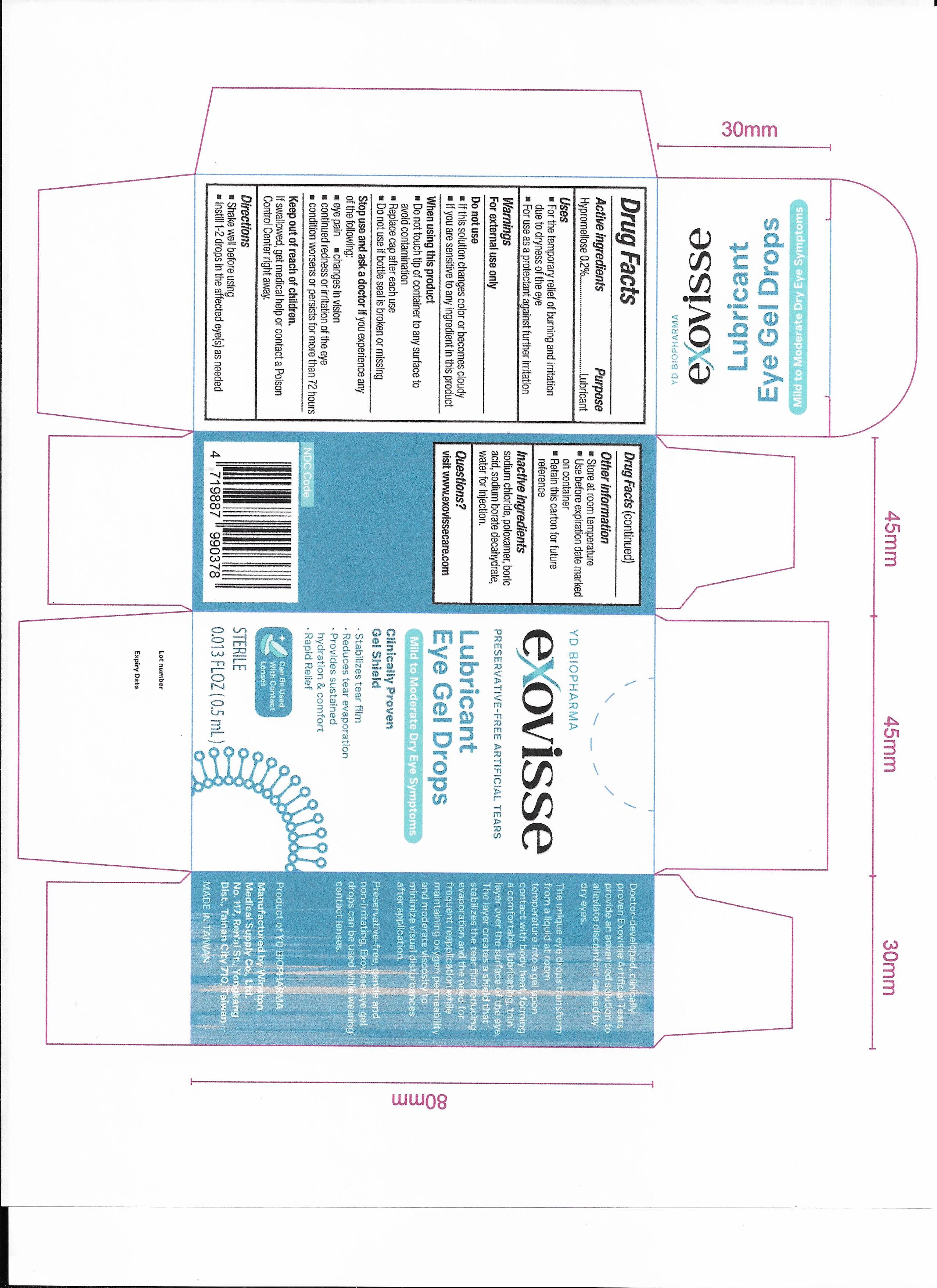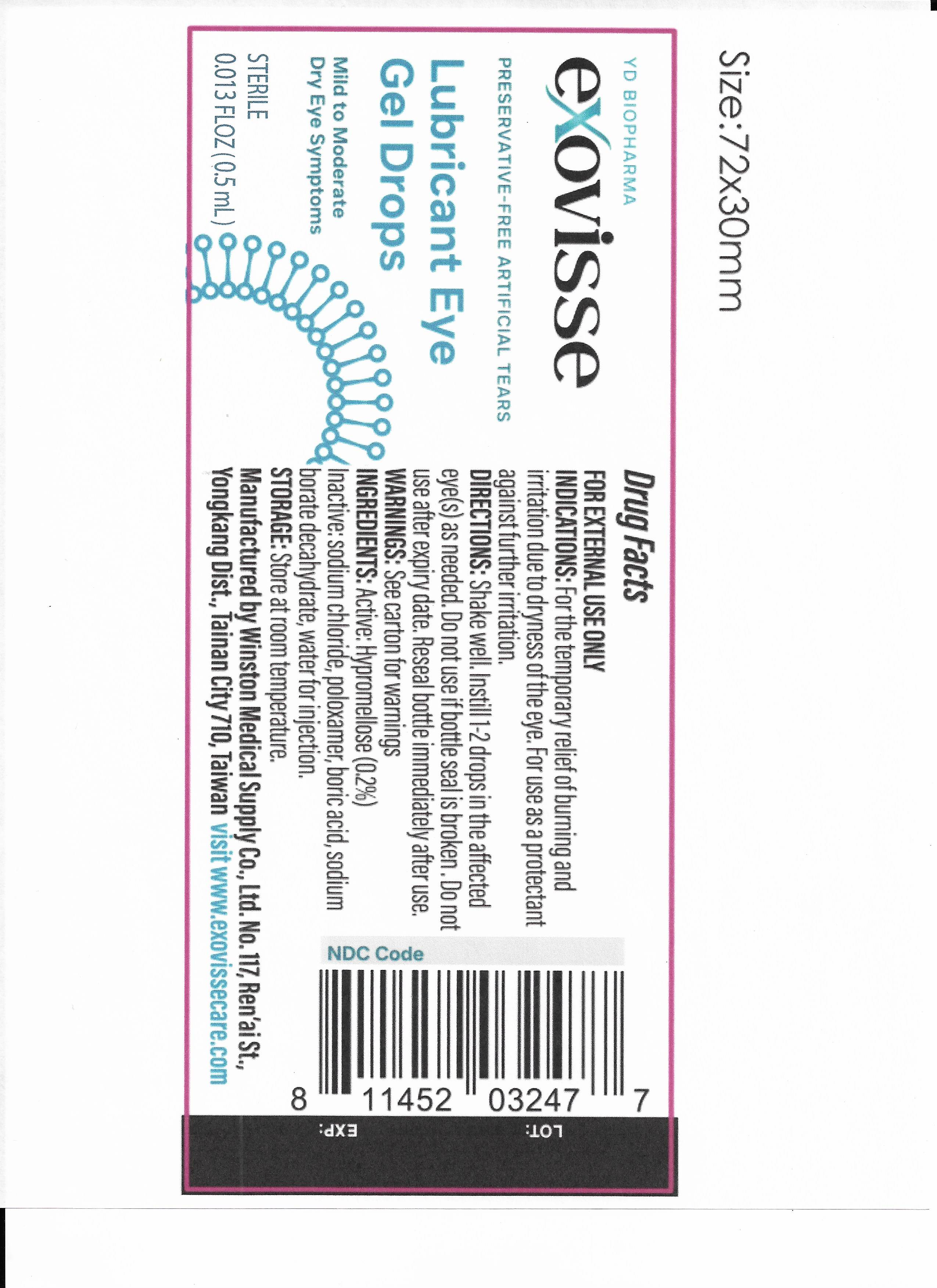 DRUG LABEL: Exovisse Preservative-Free Artificial Tears
NDC: 87106-002 | Form: GEL
Manufacturer: YD BIO USA, INC.
Category: otc | Type: HUMAN OTC DRUG LABEL
Date: 20260220

ACTIVE INGREDIENTS: HYPROMELLOSES 0.2 g/100 g
INACTIVE INGREDIENTS: SODIUM CHLORIDE; BORIC ACID; SODIUM BORATE; WATER; POLOXAMER 188

002-02

Purpose

Lubricant

Active Ingredient

Hypromellose 0.2%

Intended Use

For the temporary relief of burning and irritation due to dryness of the eye
For use as a protectant against further irritation

Warnings

For external use only

Do Not Use

If this solution changes color or becomes cloudy
If you are sensitive to any ingredient in this product

When Using

Do not touch tip of container to any surface to avoid contamination
Replace cap after each use
Do not use if bottle seal is broken or missing

Stop Use

and ask a doctor if you experience any of the following:

Eye pain
Changes in vision
Continued redness or irritation of the eye
Condition worsens or persists for more than 72 hours

Keep Out Of Reach Of Children

If swallowed, get medical help or contact a Poison Control Center right away.

Other Safety Information

Store at room temperature
Use before expiration date marked on container
Retain this carton for future reference

Inactive Ingredients

Sodium chloride, poloxamer, boric acid, sodium borate decahydrate, purified water.

DOSAGE AND ADMINISTRATION

Directions: Shake well. Instill 1-2 drops in the affected eye(s) as needed.

INDICATIONS AND USAGE

For the temporary relief of burning and irritation due to dryness of the eye.

For use as a protectant against further irritation.